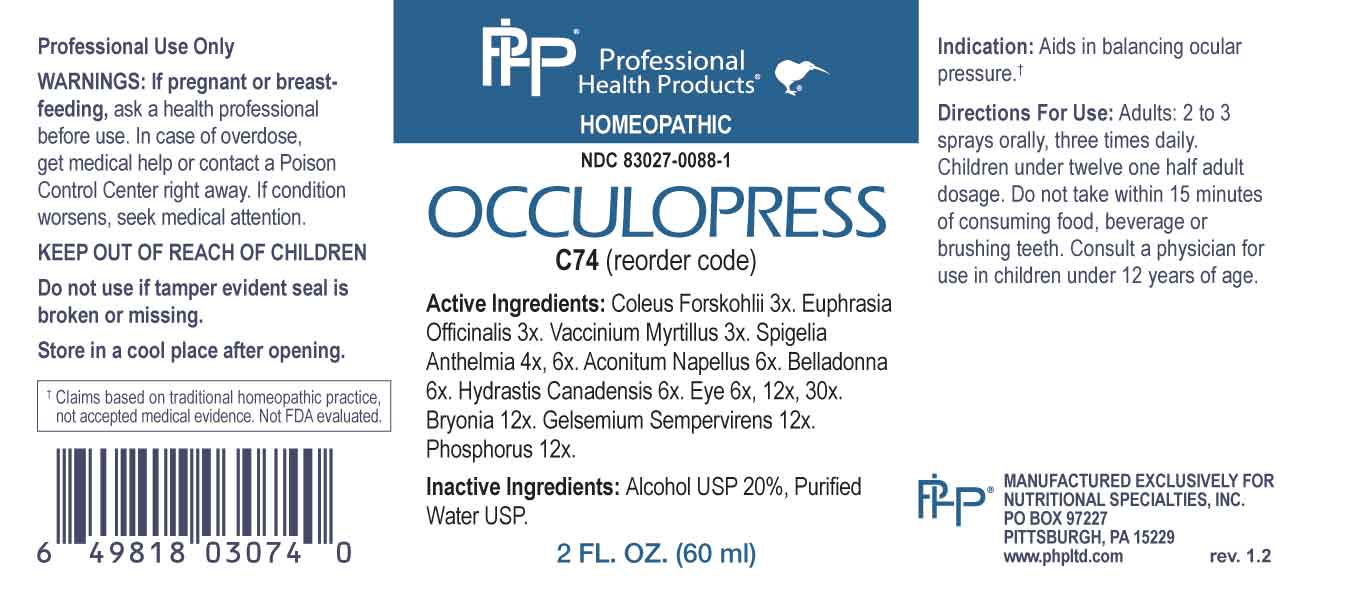 DRUG LABEL: Occulopress
NDC: 83027-0088 | Form: SPRAY
Manufacturer: Nutritional Specialties, Inc.
Category: homeopathic | Type: HUMAN OTC DRUG LABEL
Date: 20230803

ACTIVE INGREDIENTS: COLEUS BARBATUS ROOT 3 ng/1 mL; EUPHRASIA STRICTA 3 [hp_X]/1 mL; BILBERRY 3 [hp_X]/1 mL; SPIGELIA ANTHELMIA WHOLE 4 [hp_X]/1 mL; ACONITUM NAPELLUS WHOLE 6 [hp_X]/1 mL; ATROPA BELLADONNA 6 [hp_X]/1 mL; GOLDENSEAL 6 [hp_X]/1 mL; SUS SCROFA EYE 6 [hp_X]/1 mL; BRYONIA ALBA ROOT 12 [hp_X]/1 mL; GELSEMIUM SEMPERVIRENS ROOT 12 [hp_X]/1 mL; PHOSPHORUS 12 [hp_X]/1 mL
INACTIVE INGREDIENTS: WATER; ALCOHOL

DRUG FACTS:

ACTIVE INGREDIENTS:

Coleus Forskohlii 3X, Euphrasia Officinalis 3X, Vaccinium Myrtillus 3X, Spigelia Anthelmia 4X, 6X, Aconitum Napellus 6X, Belladonna 6X, Hydrastis Canadensis 6X, Eye 6X, 12X, 30X, Bryonia 12X, Gelsemium Sempervirens 12X, Phosphorus 12X.

PURPOSE:

Aids in balancing ocular pressure.†

†Claims based on traditional homeopathic practice, not accepted medical evidence. Not FDA evaluated.

WARNINGS:

Professional Use Only

If pregnant or breast-feeding, ask a health professional before use.

In case of overdose, get medical help or contact a Poison Control Center right away.

If condition worsens, seek medical attention.

KEEP OUT OF REACH OF CHILDREN

Do not use if tamper evident seal is broken or missing.

Store in a cool place after opening

KEEP OUT OF REACH OF CHILDREN:

In case of overdose, get medical help or contact a Poison Control Center right away.

DIRECTIONS:

Adults: 2 to 3 sprays orally, three times daily. Children under twelve one half adult dosage. Do not take within 15 minutes of consuming food, beverage or brushing teeth. Consult a physician for use in children under 12 years of age.

INDICATIONS:

Aids in balancing ocular pressure.†

†Claims based on traditional homeopathic practice, not accepted medical evidence. Not FDA evaluated.

INACTIVE INGREDIENTS:

Alcohol USP 20%, Purified Water USP.

QUESTIONS:

MANUFACTURED EXCLUSIVELY FOR

NUTRITIONAL SPECIALTIES, INC.

PO BOX 97227

PITTSBURG, PA 15229

www.phpltd.com

PACKAGE LABEL DISPLAY:

Professional

Health Products

HOMEOPATHIC

NDC 83027-0088-1

OCCULOPRESS

2 FL. OZ (60 ml)